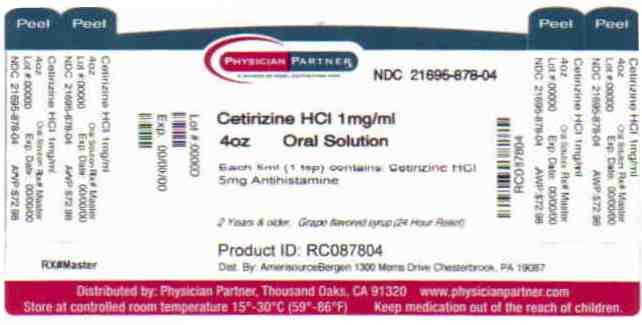 DRUG LABEL: Cetirizine
NDC: 21695-878 | Form: LIQUID
Manufacturer: Rebel Distributors Corp
Category: otc | Type: HUMAN OTC DRUG LABEL
Date: 20110215

ACTIVE INGREDIENTS: CETIRIZINE HYDROCHLORIDE 5 mg/5 mL
INACTIVE INGREDIENTS: ACETIC ACID; GLYCERIN; METHYLPARABEN; PROPYLENE GLYCOL; PROPYLPARABEN; SODIUM ACETATE; SUCROSE; WATER

Cetirizine HCl Drug Facts

Active ingredient

Cetirizine HCl 5mg

Uses

Temporarily relieves these symptoms due to hay fever or other upper respiratory allergies:

° runny nose ° sneezing ° itchy, watery eyes ° itching of the nose or throat

Warnings

Do not use if you have ever had a allergic reaction to this product or any of its ingredients or to an antihistamine containing hydroxyzine.

Ask a doctor before use if you have liver or kidney disease. Your doctor should determine if you need a different dose.

Ask a doctor or pharmacist before use if you are taking tranquilizers or sedatives.

When using this product

° drowsiness may occur ° avoid alcoholic drinks ° alcohol, sedatives and tranquilizers may increase drowsiness ° be careful when driving a motor vehicle or operating machinery

Stop use and ask a doctor if an allergic reaction to this product occurs. Seek medical help right away.

If pregnant or breast-feeding:

° if breast-feeding: not recommended

° if pregnant: ask a health professional before use.

In case of overdose, get medical help or contact a Poison Control Center right away.

Directions

Use only with enclosed dosing cup:

Adults and children 6 years and over: 1 teaspoonful (5ml) or 2 teaspoonfuls (10ml) once daily depending upon severity of symptoms; do not take more than 2 teaspoonfuls (10ml) in 24 hours.

Adults 65 years and over: 1 teaspoonful (5mo) once daily; do not take more than 1 teaspoonful (5ml) in 24 hours.

Children 2 to under 6 years of age:

1/2 teaspoonful (2.5ml) once daily. If needed, dose can be increased to a maximum of 1 teaspoonful (5mo) once daily or 1/2 teaspoonful (2.5ml) every 12 hours. Do not give more than 1 teaspoonful (5ml) in 24 hours.

Children under 2 years of age: ask a doctor

Consumers with liver or kidney disease: ask a doctor

Other Information

Do not use if carton is opened, or if printed neckband is broken or missing.

Questions or comments?

Call 1-800-719-9260

Store between 20° to 25°C (68° to 77°F)

Dosing cup should be washed and left to air dry after each use.

Inactive ingredients

acetic acid, artificial grape flavor, glycerin, methylparaben, natural banana flavor, propylene glycol, propylparaben, sodium acetate, sucrose, water

Distributed by:

AmerisourceBergen

Valley Forge, PA 19482-0959

Repackaged by:

Rebel Distributors Corp

Thousand Oaks, CA 91320